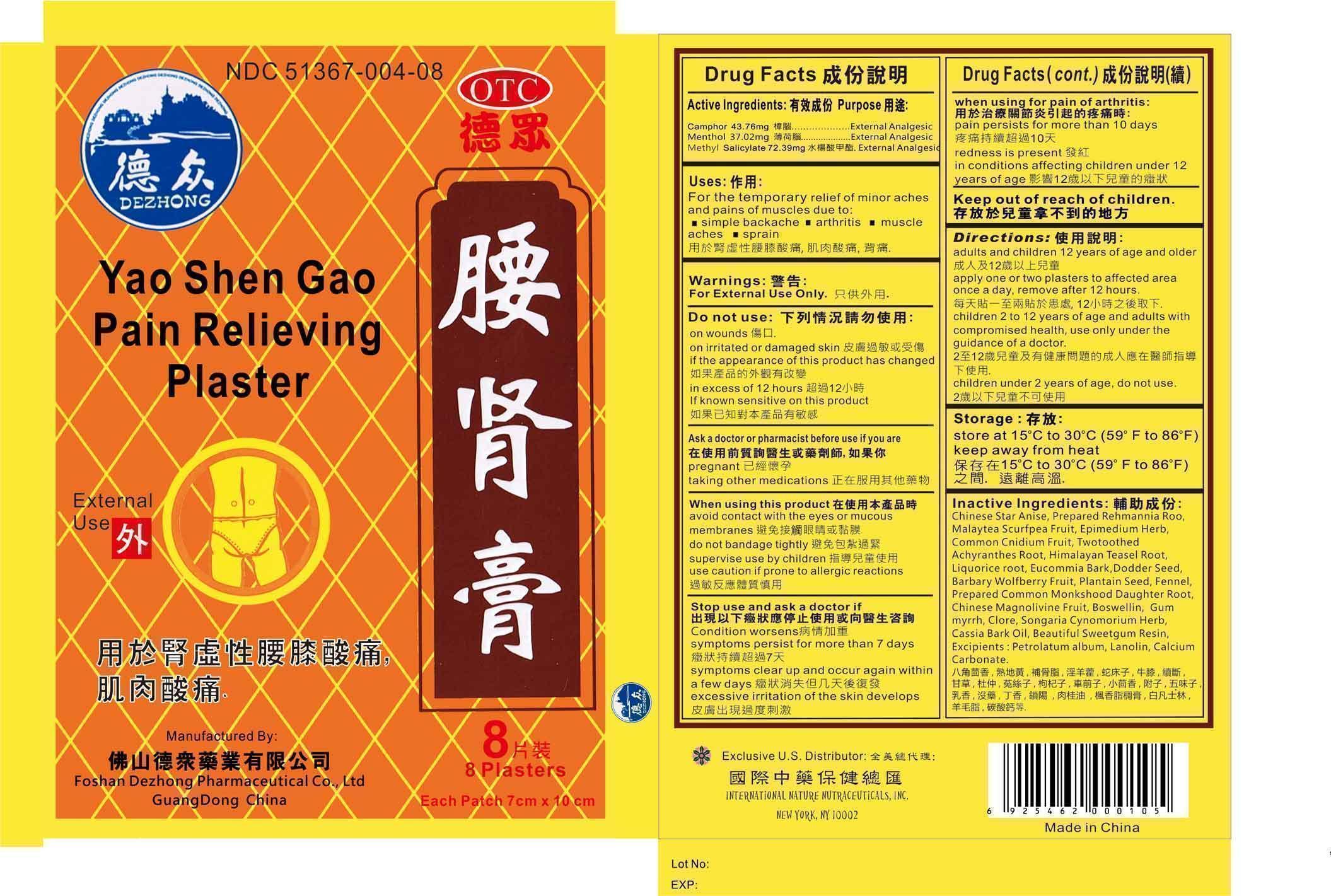 DRUG LABEL: Yao Shen Gao Pain Relieving Plaster
NDC: 51367-004 | Form: PLASTER
Manufacturer: International Nature Nutraceuticals
Category: otc | Type: HUMAN OTC DRUG LABEL
Date: 20120801

ACTIVE INGREDIENTS: CAMPHOR (NATURAL) 43.76 mg/1 1; MENTHOL 37.02 mg/1 1; METHYL SALICYLATE 72.39 mg/1 1
INACTIVE INGREDIENTS: STAR ANISE FRUIT; REHMANNIA GLUTINOSA ROOT; CULLEN CORYLIFOLIUM FRUIT; EPIMEDIUM GRANDIFLORUM WHOLE; CNIDIUM MONNIERI FRUIT; ACHYRANTHES BIDENTATA ROOT; DIPSACUS ASPER ROOT; LICORICE; EUCOMMIA ULMOIDES BARK; CUSCUTA CHINENSIS SEED; LYCIUM BARBARUM FRUIT; PLANTAGO MAJOR SEED; FENNEL; ACONITUM CARMICHAELII ROOT; SCHISANDRA CHINENSIS FRUIT; INDIAN FRANKINCENSE; MYRRH; SYZYGIUM AROMATICUM WHOLE; CHINESE CINNAMON OIL; LIQUIDAMBAR STYRACIFLUA RESIN; PETROLATUM; LANOLIN; CALCIUM CARBONATE

Drug Facts

Active Ingreidents

Camphor- 43.76 mg

Menthol- 37.02 mg

Methyl Salicylate- 72.39 mg

Uses

For the temporary relief of minor aches and pains of muscles due to:

Simple backache

Arthritis

Muscle aches

Sprains

Warnings

For external use only

Do Not Use

On wounds

On irritated or damaged skin

If the appearance of this product has changed

In excess of 12 hours

If known sensitive to this product

Ask a Doctor or Pharmacist before use if you are

Pregnant

Taking other medications

When Using this Product

Acoid contact with eyes or mucous membranes

Do not bandage tightly

Supervise use by children

Use caution if prone to allergic reactions

Stop Use and Ask a Doctor if

Condition worsens

Sumptoms persit for more than 7 days

Symptoms clear up and occur again within a few days

Excessive irritation of the skin develops

When Using for Pain of Arthritis

Pain persists for more than 10 days

Redness is present

In conditions affecting children under 12 years of age

Directions

Adults and children 12 years of age and older- apply one or two plasters to affected area once a day, remove after 12 hours

Children 2 to 12 years of age and adults with compromised health- use only under the guidance of a doctor

Children under 2 years of age- do not use

Storage

Store at 15°C to 30°C (59°F to 86°F)
Keep away from Heat
Store in a dry place

Inactive Ingredients

Chinese Star Anise, Prepared Rehmannia Root, Malaytea Scurfpea Fruit, Epimedium Herb, Common Cnidium Fruit, Twotothed Achranthes Root, Himalayan Teasel Root, Liquorice Root, Eucommia Bark, Dodder Seed, Barbary Wolfberry Fruit, Boswellin, Gum Myrrh, Clore, Songaria Cynomorium Herb, Cassia Bark Oil, Beautiful Sweetgum Resin

Excipients:

Petrolatum album, Lanolin, Calcium Carbonate